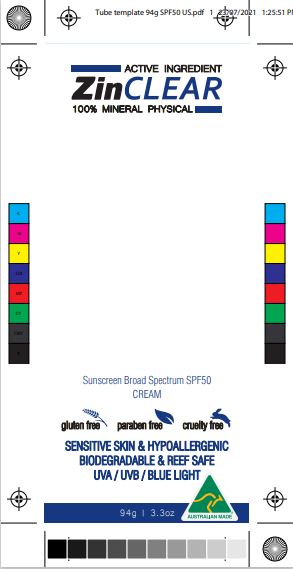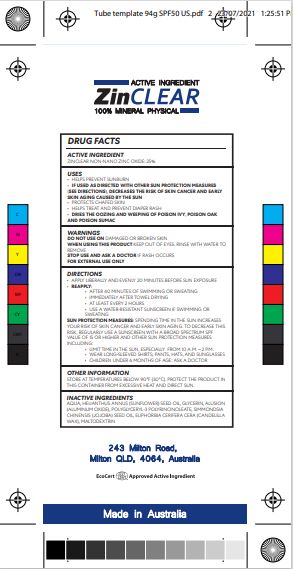 DRUG LABEL: ORGANIC ZINCLEAR SUNSCREEN
NDC: 80982-009 | Form: LOTION
Manufacturer: ASTIVITA LIMITED
Category: otc | Type: HUMAN OTC DRUG LABEL
Date: 20210729

ACTIVE INGREDIENTS: ZINC OXIDE 25 g/100 g
INACTIVE INGREDIENTS: ALUMINUM OXIDE; MALTODEXTRIN; CANDELILLA WAX; SUNFLOWER OIL; JOJOBA OIL; POLYGLYCERYL-3 RICINOLEATE; WATER; GLYCERIN

Organic ZinClear Sunscreen